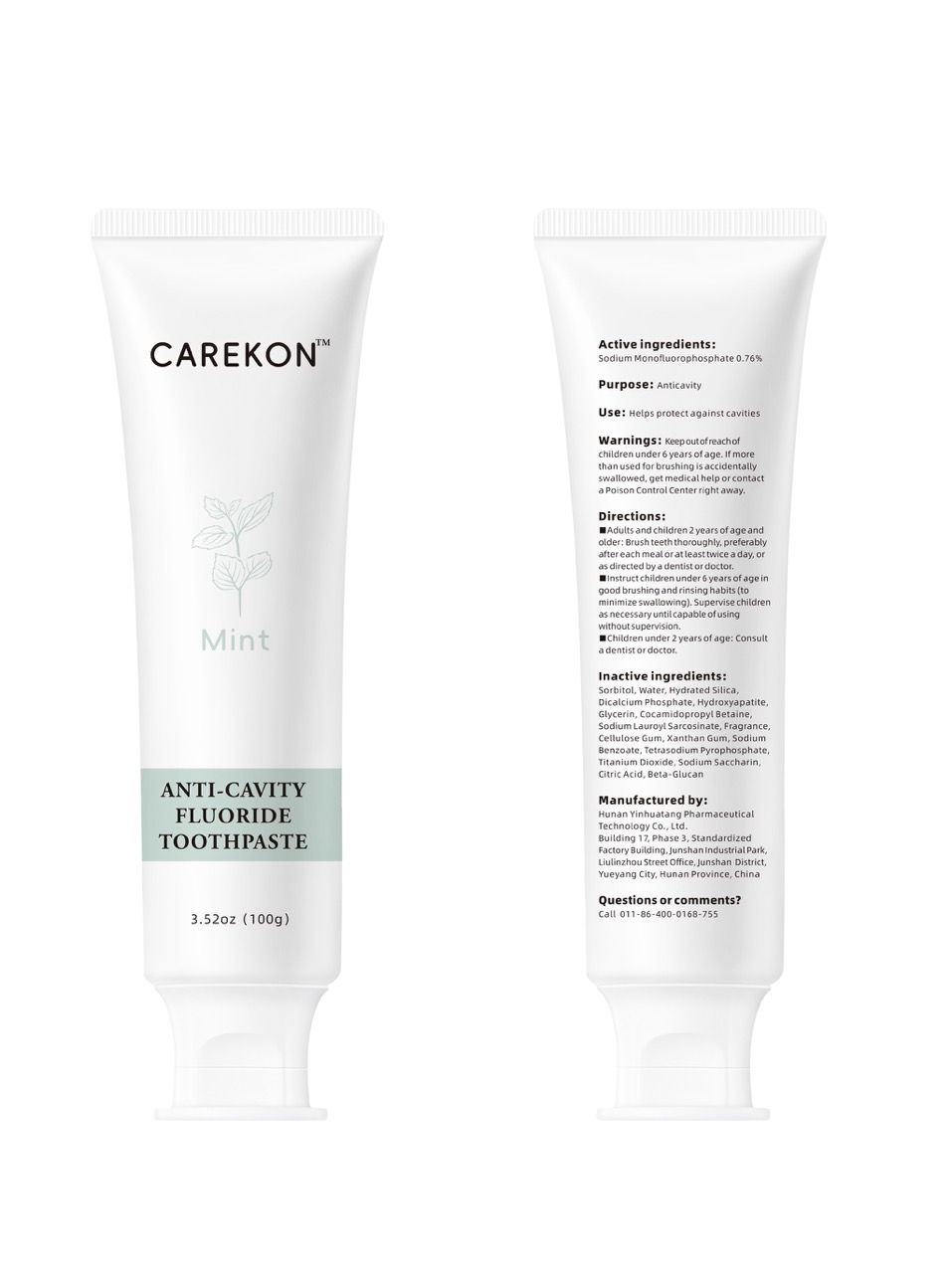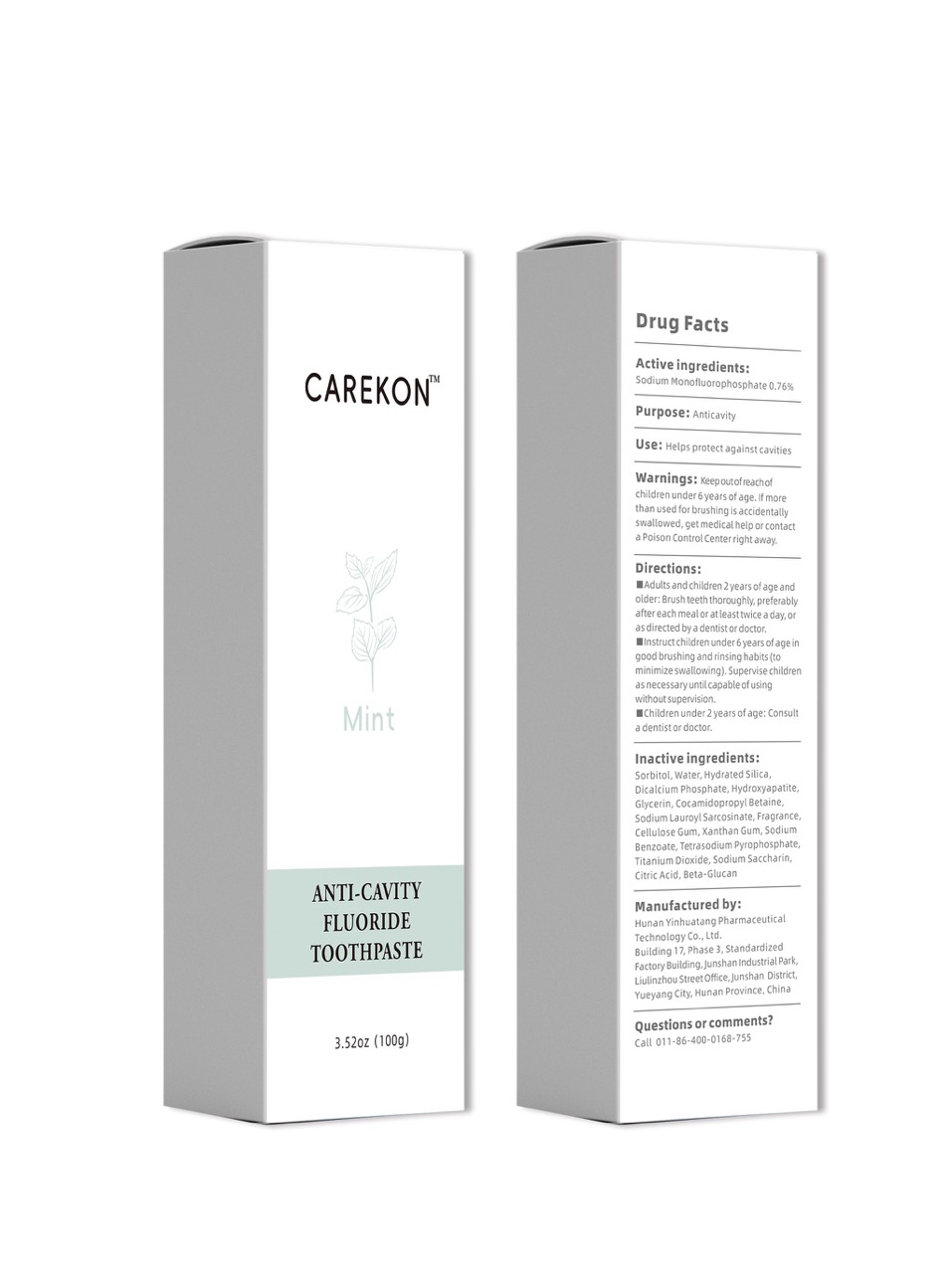 DRUG LABEL: CAREKON ANTI-CAVITY FLUORIDE
NDC: 84345-086 | Form: PASTE
Manufacturer: Hunan Yinhuatang Pharmaceutical Technology Co., Ltd.
Category: otc | Type: HUMAN OTC DRUG LABEL
Date: 20250829

ACTIVE INGREDIENTS: SODIUM MONOFLUOROPHOSPHATE 0.76 g/100 g
INACTIVE INGREDIENTS: TETRASODIUM PYROPHOSPHATE; COCAMIDOPROPYL BETAINE; FRAGRANCE 13576; XANTHAN GUM; TITANIUM DIOXIDE; HYDROXYAPATITE; HYDRATED SILICA; SODIUM LAUROYL SARCOSINATE; 1,3-BETA-GLUCAN SYNTHASE COMPONENT FKS1; CELLULOSE GUM; WATER; DICALCIUM PHOSPHATE; GLYCERIN; CITRIC ACID; SODIUM BENZOATE; SORBITOL; SODIUM SACCHARIN

ACTIVE INGREDIENT

Sodium monofluorophosphate 0.76% (0.76g/100g)

PURPOSE

Anticavity

Keep out of reach of children under 6 years of age

INDICATIONS AND USAGE

Adults and children 2 years of age and older: Brush teeth thoroughly, preferably after each meal or at least twice a day, or as directed by a dentist or doctor.

Instruct children under 6 years of age in good brushing and rinsing habits (to minimize swallowing). Supervise children as necessary until capable of using without supervision.

Children under 2 years of age: Consult a dentist or doctor.

Keep out of reach of children under 6 years of age. If more than used for brushing is accidentally swallowed, get medical help or contact a Poison Control Center right away.

DOSAGE AND ADMINISTRATION

Adults and children 2 years of age and older: Brush teeth thoroughly, preferably after each meal or at least twice a day, or as directed by a dentist or doctor.

Instruct children under 6 years of age in good brushing and rinsing habits (to minimize swallowing).

INACTIVE INGREDIENT

Sorbitol, Water, Hydrated Silica, Dicalcium Phosphate, Hydroxyapatite, Glycerin, Cocamidopropyl Betaine, Sodium Lauroyl Sarcosinate, Fragrance, Cellulose Gum, Xanthan Gum, Sodium Benzoate, Tetrasodium Pyrophosphate, Titanium Dioxide, Sodium Saccharin, Citric Acid, Beta-Glucan